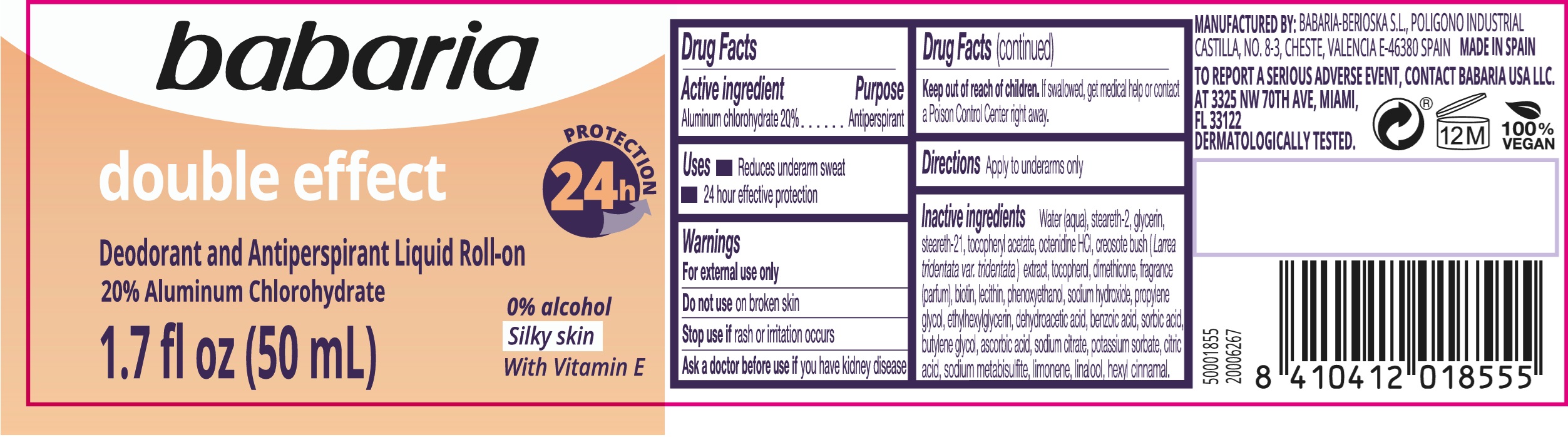 DRUG LABEL: Babaria Double Effect Deodorant and Antiperspirant Liquid Roll-On
NDC: 78283-003 | Form: EMULSION
Manufacturer: BERIOSKA SL
Category: otc | Type: HUMAN OTC DRUG LABEL
Date: 20251220

ACTIVE INGREDIENTS: ALUMINUM CHLOROHYDRATE 200 mg/1 mL
INACTIVE INGREDIENTS: WATER; STEARETH-2; LARREA TRIDENTATA WHOLE; GLYCERIN; STEARETH-21; .ALPHA.-TOCOPHEROL ACETATE; OCTENIDINE HYDROCHLORIDE; TOCOPHEROL; DIMETHICONE; BIOTIN; PHENOXYETHANOL; SODIUM HYDROXIDE; PROPYLENE GLYCOL; ETHYLHEXYLGLYCERIN; DEHYDROACETIC ACID; BENZOIC ACID; SORBIC ACID; BUTYLENE GLYCOL; ASCORBIC ACID; SODIUM CITRATE; POTASSIUM SORBATE; CITRIC ACID MONOHYDRATE; SODIUM METABISULFITE; LIMONENE, (+)-; LINALOOL, (+/-)-; .ALPHA.-HEXYLCINNAMALDEHYDE

Babaria Double Effect Deodorant and Antiperspirant Liquid Roll-On

Active ingredient

Aluminum chlorohydrate 20%

Purpose

Antiperspirant

Uses

- Reduces underarm sweat
- 24 hour effective protection

Warnings

For external use only

Do not use

on broken skin

Stop use if

rash or irritation occurs

Ask a doctor before use if

you have kidney disease

Keep out of reach of children.

If swallowed, get medical help or contact a Posion Control Center right away.

Directions

Apply to underarms only

Inactive ingredients

Water (aqua), steareth-2, glycerin, steareth-21, tocopherol acetate octenidine HCL, creosote bush (Larrea tridentata var, tridentata) extract, tocopherol, dimethicone fragrance (parfum), biotin, lecithin, phenoxyethanol, sodium hydroxide, propylene glycol, ethylhexylglycerin, dehydroacetic acid, benzoic acid, sorbic acid, butylene glycol, ascorbic acid, sodium citrate, potassium sorbate, citric acid, sodium metabisulfite, limonene, linalool, hexyl cinnamal.